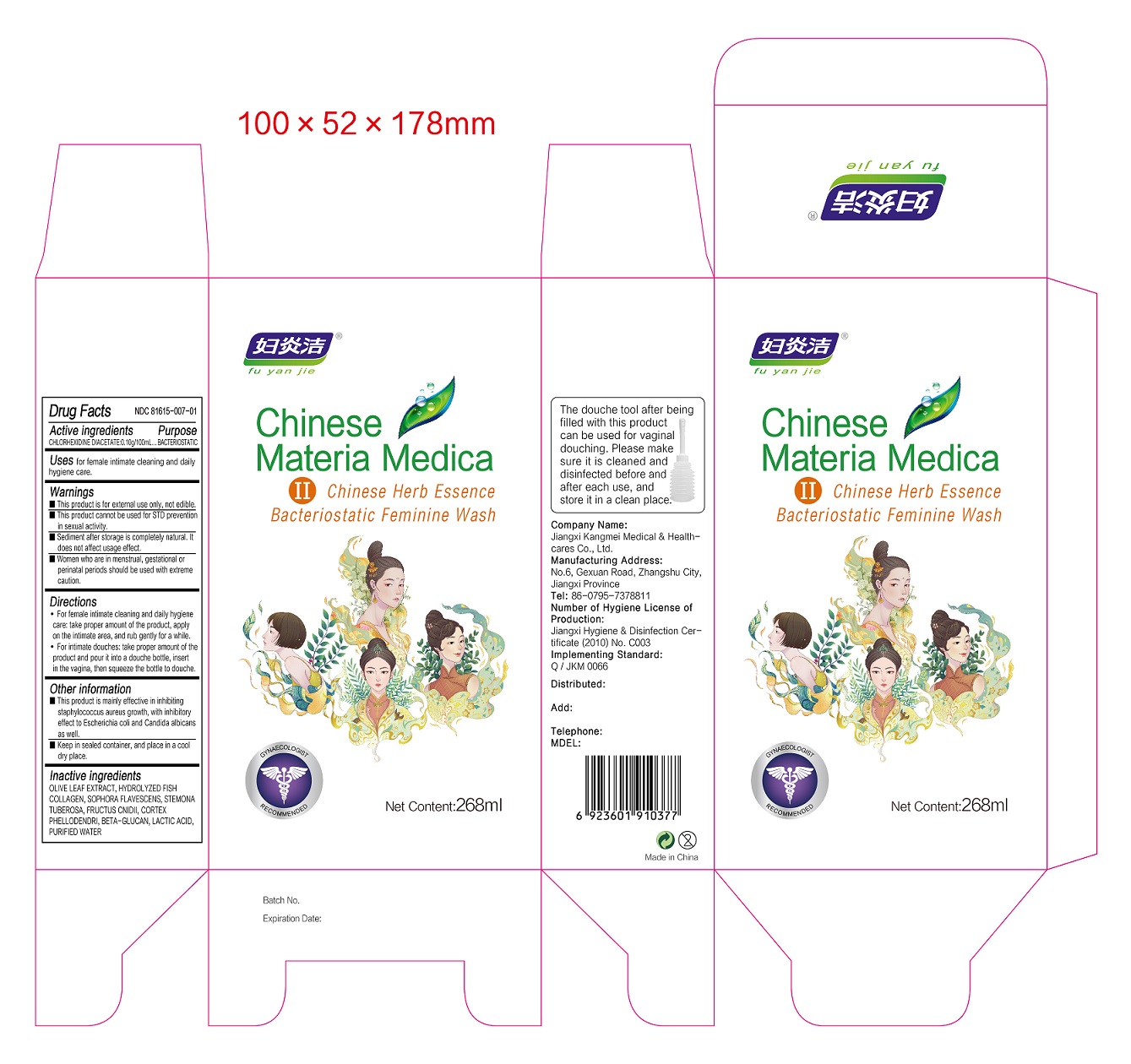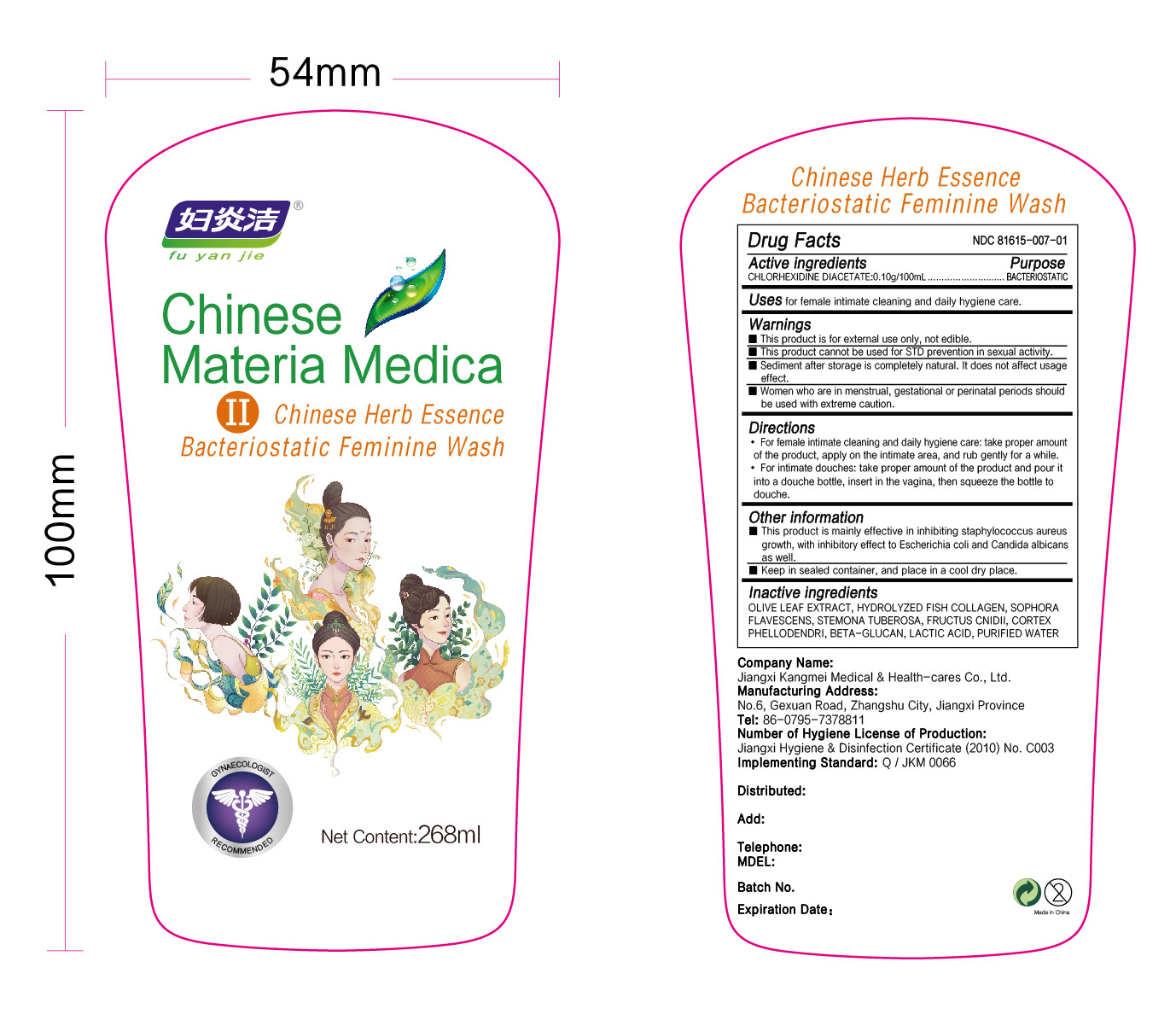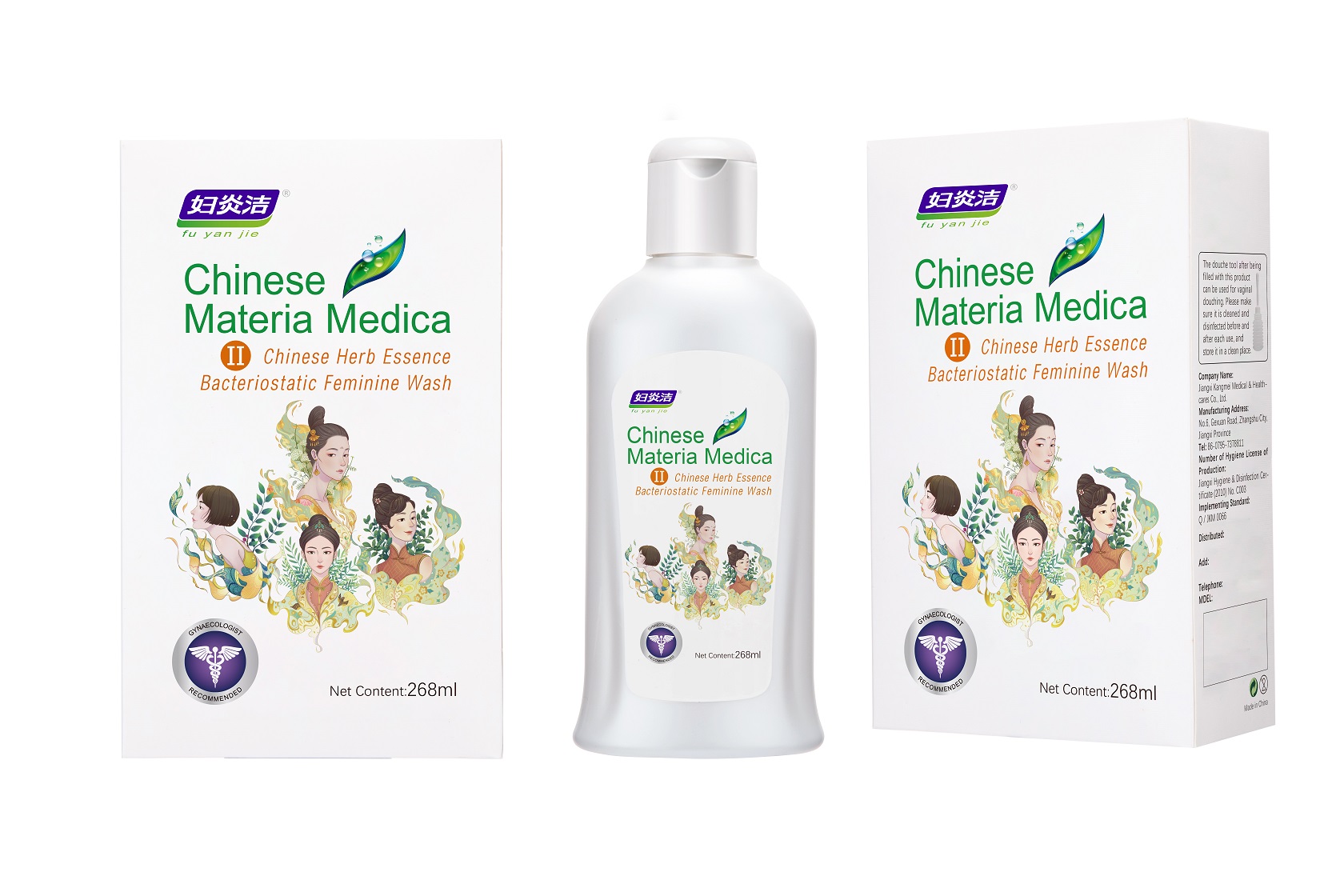 DRUG LABEL: CHINESE HERB ESSENCE BACTERIOSTATIC FEMININE WASH
NDC: 81615-007 | Form: LIQUID
Manufacturer: Jiangxi Renhetang pharmaceutical chain Co., Ltd.
Category: otc | Type: HUMAN OTC DRUG LABEL
Date: 20210420

ACTIVE INGREDIENTS: CHLORHEXIDINE ACETATE 0.1 g/100 mL
INACTIVE INGREDIENTS: OLEA EUROPAEA LEAF; HYDROLYSED MARINE COLLAGEN (ENZYMATIC; 2000 MW); WATER; SOPHORA FLAVESCENS ROOT; OSTHOL; PHELLODENDRON CHINENSE WHOLE; LACTIC ACID; STEMONA TUBEROSA ROOT; CURDLAN

CHINESE HERB ESSENCE BACTERIOSTATIC FEMININE WASH

CHINESE HERB ESSENCE BACTERIOSTATIC FEMININE WASH

Active Ingredient(s)

CHLORHEXIDINE DIACETATE 0.10g/100mL

Purpose

BACTERIOSTATIC

Use

Uses for female intimate cleaning and daily hygiene care.

Warnings

This product is for external use only, not edible.

This product cannot be used for STD prevention in sexual activity.

Sediment after storage is completely natural. It does not affect usage effect.

Women who are in menstrual, gestational or perinatal periods should be used with extreme caution.

When using this product keep out of eyes, ears, and mouth. In case of contact with eyes, rinse eyes thoroughly with water.
Stop use and ask a doctor if irritation or rash occurs. These may be signs of a serious condition.
Keep out of reach of children. If swallowed, get medical help or contact a Poison Control Center right away.

Stop use and ask a doctor if irritation or rash occurs. These may be signs of a serious condition.

Keep out of reach of children. If swallowed, get medical help or contact a Poison Control Center right away.

Directions

1.For female intimate cleaning and daily hygiene care: take proper amount of the product, apply on the intimate area, and rub gently for a while.
2.For intimate douches: take proper amount of the product and pour it into a douche bottle, insert in the vagina, then squeeze the bottle to douche.

Other information

This product is mainly effective in inhibiting staphylococcus aureus growth, with inhibitory effect to Escherichia coli and Candida albicans as well.

Keep in sealed container, and place in a cool dry place.

Inactive ingredients

OLIVE LEAF EXTRACT
HYDROLYZED FISH COLLAGEN
SOPHORA FLAVESCENS
STEMONA TUBEROSA
FRUCTUS CNIDII
CORTEX PHELLODENDRI
BETA-GLUCAN
LACTIC ACID
PURIFIED WATER